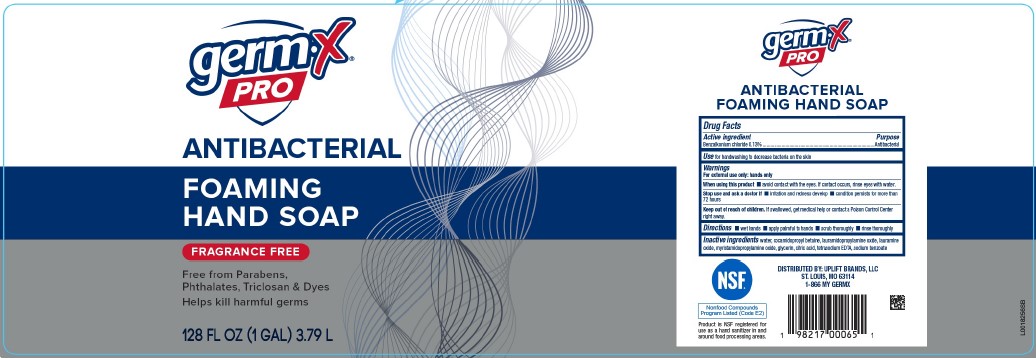 DRUG LABEL: Foaming Hand
NDC: 83986-224 | Form: SOAP
Manufacturer: UpLift Brands, LLC
Category: otc | Type: HUMAN OTC DRUG LABEL
Date: 20250414

ACTIVE INGREDIENTS: BENZALKONIUM CHLORIDE 1.3 mg/1 mL
INACTIVE INGREDIENTS: WATER; COCAMIDOPROPYL BETAINE; LAURAMIDOPROPYLAMINE OXIDE; LAURAMINE OXIDE; MYRISTAMIDOPROPYLAMINE OXIDE; GLYCERIN; CITRIC ACID MONOHYDRATE; EDETATE SODIUM; SODIUM BENZOATE

Germ-X 224.000/224AA
Antibacterial Foaming Hand Soap

Claims

germ-X

PRO

ANTIBACTERIAL

FOAMING HAND SOAP

Active ingredient

Benzalkonium chloride 0.13%

Purpose

Antibacterial

Use

for handwashing to decrease bacteria on the skin

Warnings

For external use only: hands only

When using this product

- avoid contact with eyes. If contact occurs, rinse eyes thoroughly with water.

Stop use and ask a doctor if

- irritation and redness develop
- condition persists for more than 72 hours

Keep out of reach of children.

If swallowed, get medical help or contact a Poison Control Center right away.

Directions

- wet hands
- apply palmful to hands
- scrub thoroughly
- rinse thoroughly

Inactive ingredients

water, cocamidopropyl betaine, lauramidopropylamine oxide, lauramine oxide, myristamidopropylamine oxide, glycerin, citric acid, tetrasodium EDTA, sodium benzoate

Claims

NSF

Nonfood Compounds

Program Listed (Code E2)

Product is NSF registered for us as a hand sanitizer in and around food processing areas.

Adverse event

DISTRIBUTED BY:

UPLIFT BRANDS, LLC

ST. LOUIS, MO 63114

1-866 MY GERMX

Principal display panel

germ-X®

PRO

ANTIBACTERIAL

FOAMING

HAND SOAP

FRAGRANCE FREE

Free from Parabens, Phthalates, Triclosan & Dyes

Helps kill harmful germs

128 FL OZ (1 GAL) 3.79 L